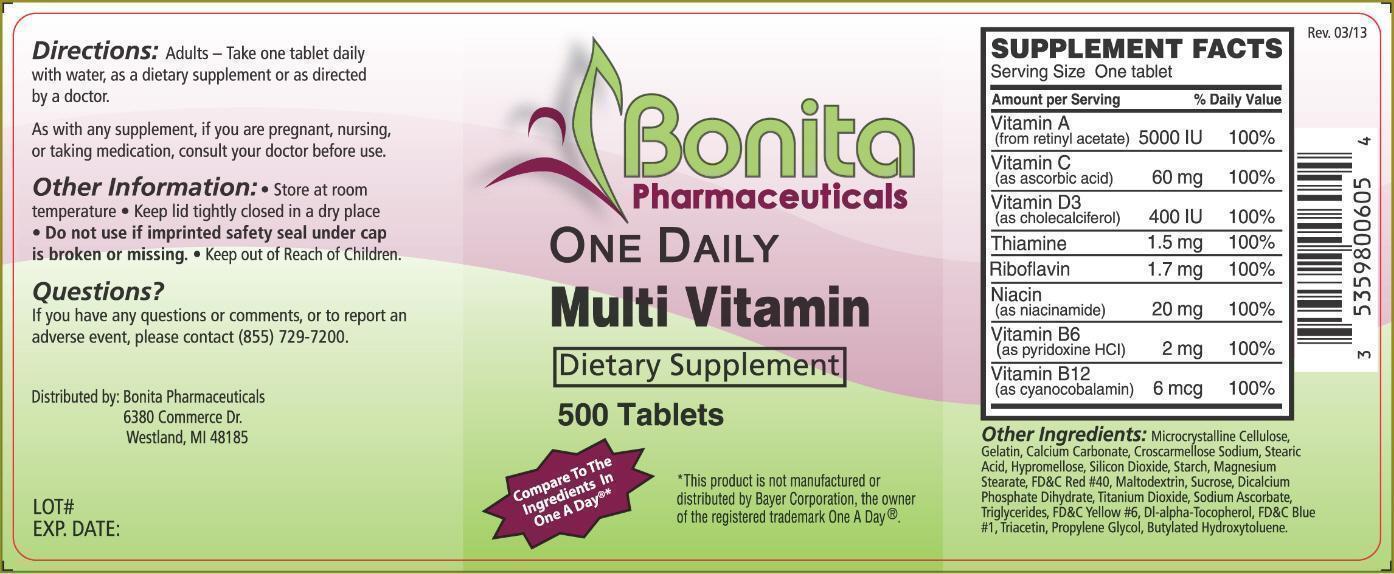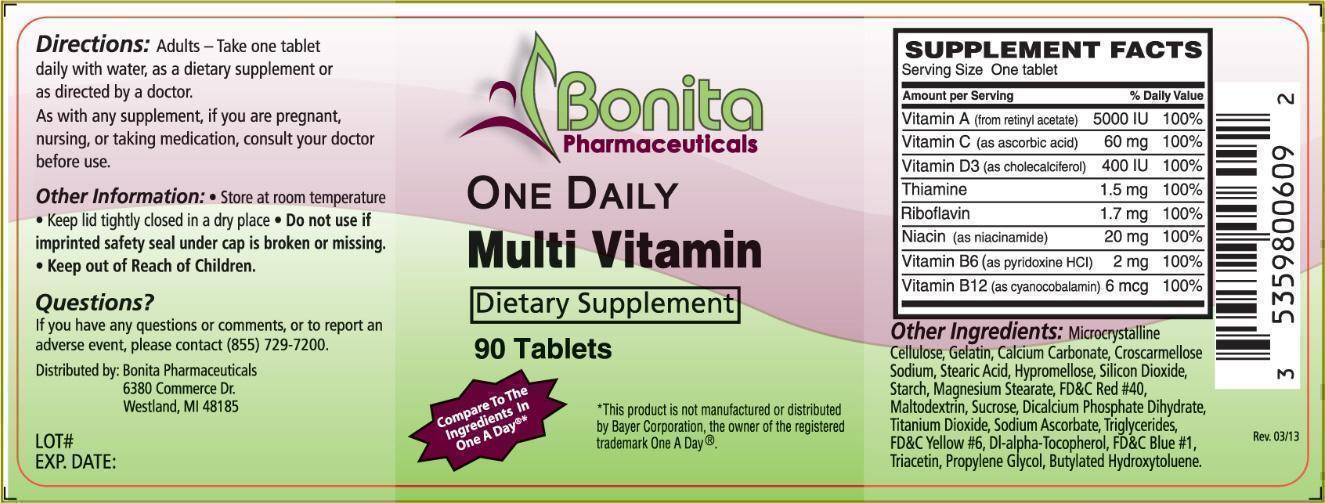 DRUG LABEL: Multivitamins
NDC: 53598-006 | Form: TABLET, FILM COATED
Manufacturer: Bonita Pharmaceuticals LLC
Category: other | Type: DIETARY SUPPLEMENT
Date: 20130614

ACTIVE INGREDIENTS: VITAMIN A ACETATE 5000 [iU]/1 1; ASCORBIC ACID 60 mg/1 1; CHOLECALCIFEROL 400 [iU]/1 1; THIAMINE 1.5 mg/1 1; RIBOFLAVIN 1.7 mg/1 1; NIACINAMIDE 20 mg/1 1; PYRIDOXINE HYDROCHLORIDE 2 mg/1 1; CYANOCOBALAMIN 6 ug/1 1
INACTIVE INGREDIENTS: CELLULOSE, MICROCRYSTALLINE; GELATIN; CALCIUM CARBONATE; CROSCARMELLOSE SODIUM; STEARIC ACID; HYPROMELLOSES; SILICON DIOXIDE; STARCH, CORN; MAGNESIUM STEARATE; FD&C RED NO. 40; MALTODEXTRIN; SUCROSE; CALCIUM PHOSPHATE, DIBASIC, DIHYDRATE; TITANIUM DIOXIDE; SODIUM ASCORBATE; MEDIUM-CHAIN TRIGLYCERIDES; FD&C YELLOW NO. 6; .ALPHA.-TOCOPHEROL, DL-; FD&C BLUE NO. 1; TRIACETIN; PROPYLENE GLYCOL; BUTYLATED HYDROXYTOLUENE

One Daily Multi Vitamin Dietary Supplement

DESCRIPTION:

One Daily Multi Vitamin is a dietary supplement containing vitamins within a red, film coated tablet.

SUPPLEMENT FACTS:

Serving Size: One Tablet

VITAMINS | Amount per Serving | % Daily Value
Vitamin A (from retinyl acetate) | 5000 IU | 100%
Vitamin C (as ascorbic acid) | 60 mg | 100%
Vitamin D3 (as cholecalciferol) | 400 IU | 100%
Thiamine | 1.5 mg | 100%
Riboflavin | 1.7 mg | 100%
Niacin (as niacinamide) | 20 mg | 100%
Vitamin B6 (as pyridoxine HCl) | 2 mg | 100%
Vitamin B12 (as cyanocobalamin) | 6 mcg | 100%

OTHER INGREDIENTS:

Microcrystalline Cellulose, Gelatin, Calcium Carbonate, Croscarmellose Sodium, Stearic Acid, Hypromellose, Silicon Dioxide, Starch, Magnesium Stearate, FD&C Red #40, Maltodextrin, Sucrose, Dicalcium Phosphate Dihydrate, Titanium Dioxide, Sodium Ascorbate, Triglycerides, FD&C Yellow #6, Dl-alpha-Tocopherol, FD&C Blue #1, Triacetin, Propylene Glycol, Butylated Hydroxytoluene.

DIRECTIONS:

Adults - Take one tablet daily with water, as a dietary supplement or as directed by a doctor.

WARNINGS:

As with any supplement, if you are pregnant, nursing, or talking medication, consult your doctor before use.

OTHER INFORMATION:

- Store at room temperature
- Keep lid tightly closed in a dry place
- Do not use if imprinted safety seal under cap is broken or missing.
- Keep out of reach of children

QUESTIONS?

If you have any questions or comments, or to report an adverse event, please contact (855) 729-7200.

DISTRIBUTED BY:

Bonita Pharmaceuticals

6380 Commerce Dr.

Westland, MI 48185